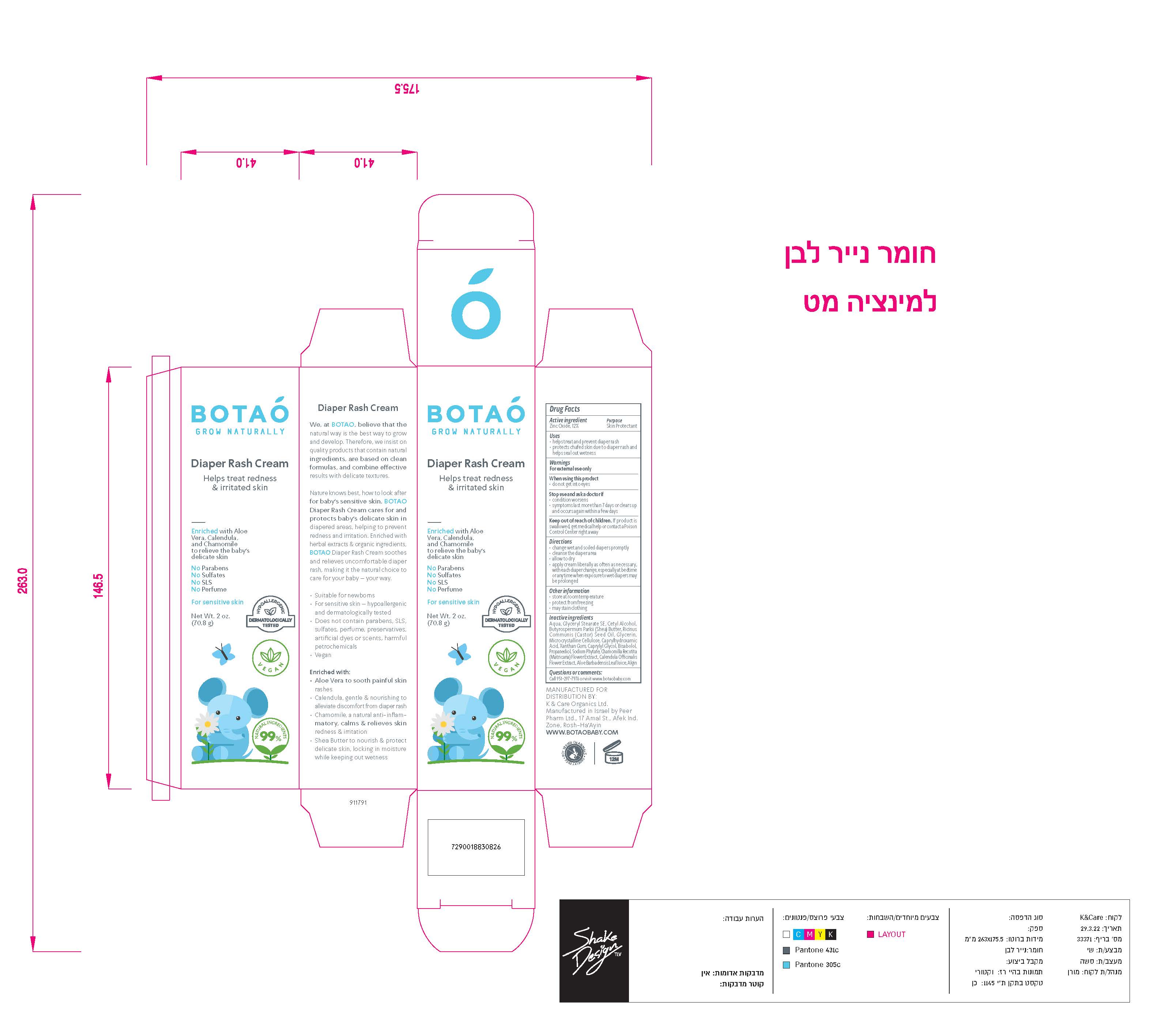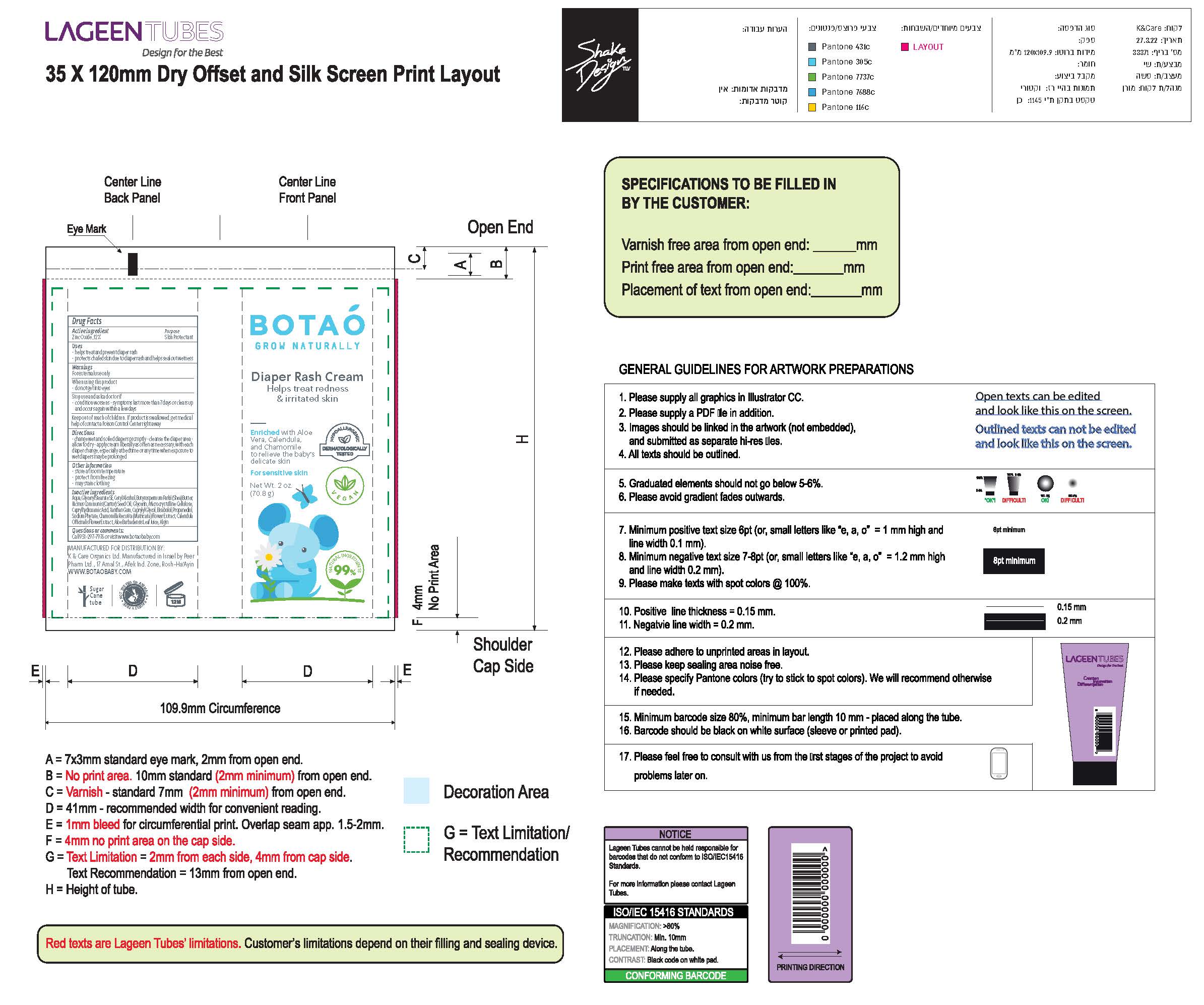 DRUG LABEL: Botao Baby Diaper Rash Cream
NDC: 69435-1501 | Form: CREAM
Manufacturer: Peer Pharm Ltd.
Category: otc | Type: HUMAN OTC DRUG LABEL
Date: 20260112

ACTIVE INGREDIENTS: ZINC OXIDE 9 g/71 g
INACTIVE INGREDIENTS: HEXASODIUM PHYTATE; CAPRYLYL GLYCOL; ALGINIC ACID; ALOE; MICROCRYSTALLINE CELLULOSE; WATER; GLYCERYL STEARATE SE; CETYL ALCOHOL; CAPRYLHYDROXAMIC ACID; BUTYROSPERMUM PARKII (SHEA) BUTTER UNSAPONIFIABLES; RICINUS COMMUNIS SEED; CASTOR OIL; GLYCERIN; PROPANEDIOL 1-PHOSPHATE; CHAMOMILE; .BETA.-BISABOLOL; XANTHAN GUM; CALENDULA OFFICINALIS FLOWER

Botao Baby Diaper Rash Cream

Active Ingredients(in each 30 ml)

Zinc Oxide 12%

Purpose

Sunscreen

Uses

- Helps treat and prevent diaper rash
- Protects chafed skin due to diaper rash and helps seal out wetness

warnings

- For external use only.

Do not use

- on damaged or broken skin.

When using this product,

- Keep out of eyes. Rinse with water to remove.

Stop use and ask a doctor

- if rash or irritation develops and lasts.

Keep out of reach of children.

If swallowed, call a poison control center or get medical help right away.

Directions

Change Wet and Soiled Diapers Promptly

Cleanse the diaper area

Allow to dry

Apply cream liberally as often as necessary , with each diaper change , especially at bedtime or anytime when exposure to wet diapers may be prolonged.

Inactive Ingredients

Coconut Alkanes, Cocos Nucifera (Virgin Coconut) Oil, Caprylic/Capric Triglyceride, Aloe Barbadensis Leaf Juice, Ricinus Communis (Castor) Seed Oil*, Ethyl Macadamiate, Shea Butter Ethyl Ester, Glycerin*, Polyglyceryl Esters, Polyhydroxystearic Acid, Citrus Aurantium Dulcis (Orange) Peel Wax, Simmondsia Chinensis (Jojoba) Seed Oil*, Jojoba Esters, Coco-Caprylate/Caprate, Copernicia Cerifera (Carnauba) Wax*, Butyrospermum Parkii (Shea Butter) Fruit*, Tocopherol (Vitamin E), Capric Acid, Silica, Disteardimonium Hectorite, Kaolin, Argania Spinosa (Argan) Kernel Oil, Rosa Canina Seed (Rosehip) Oil, Lavandula Angustifolia (Lavender) Oil, Olea Europaea (Olive) Oil, Origanum Vulgare (Oregano) Leaf Extract,
Tocopheryl Acetate, Basabolol, Malic Acid. May Contain: Iron Oxides.
*Certified Organic

Other Information

- Store in room temparture
- protect from freezing
- may stain clothing